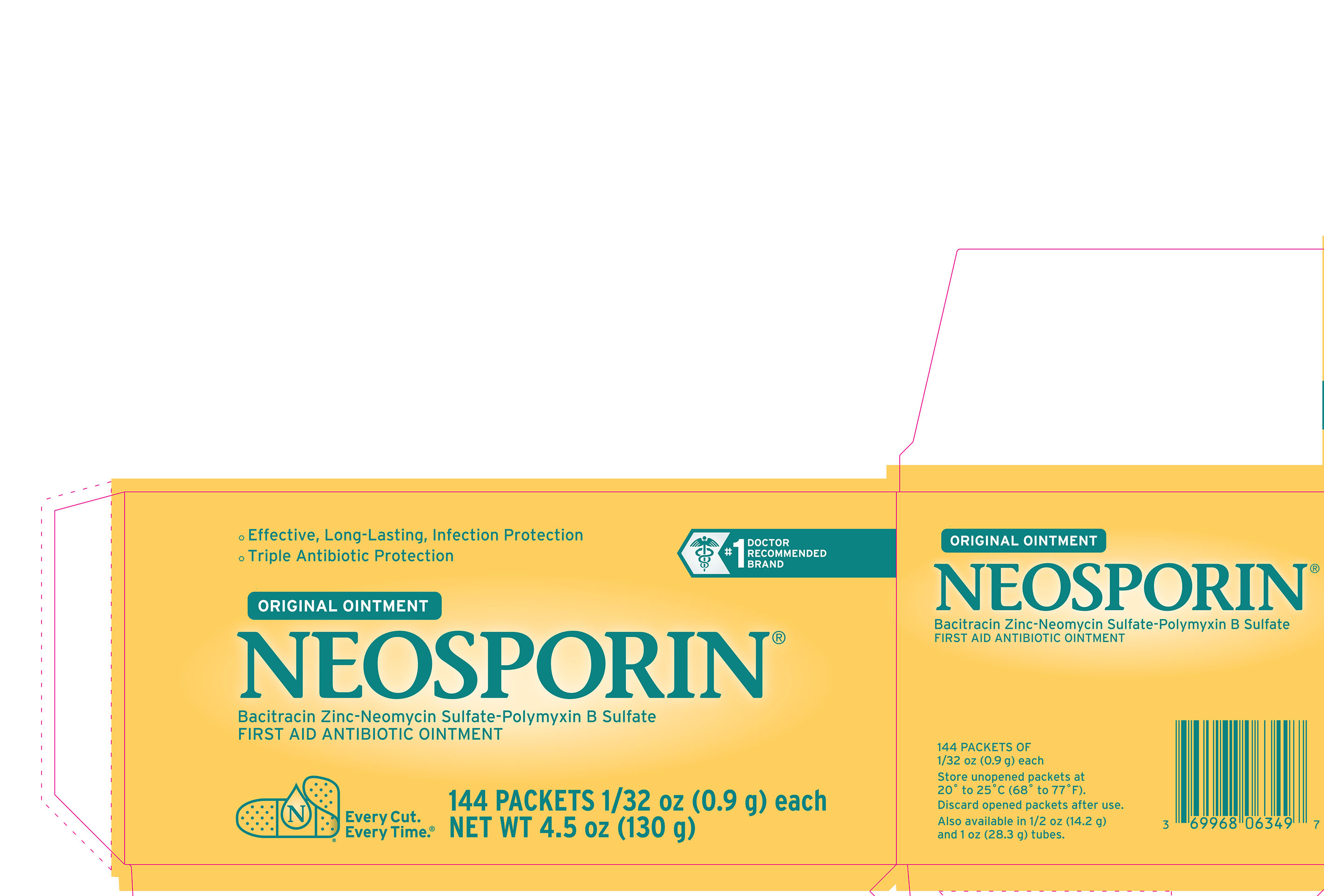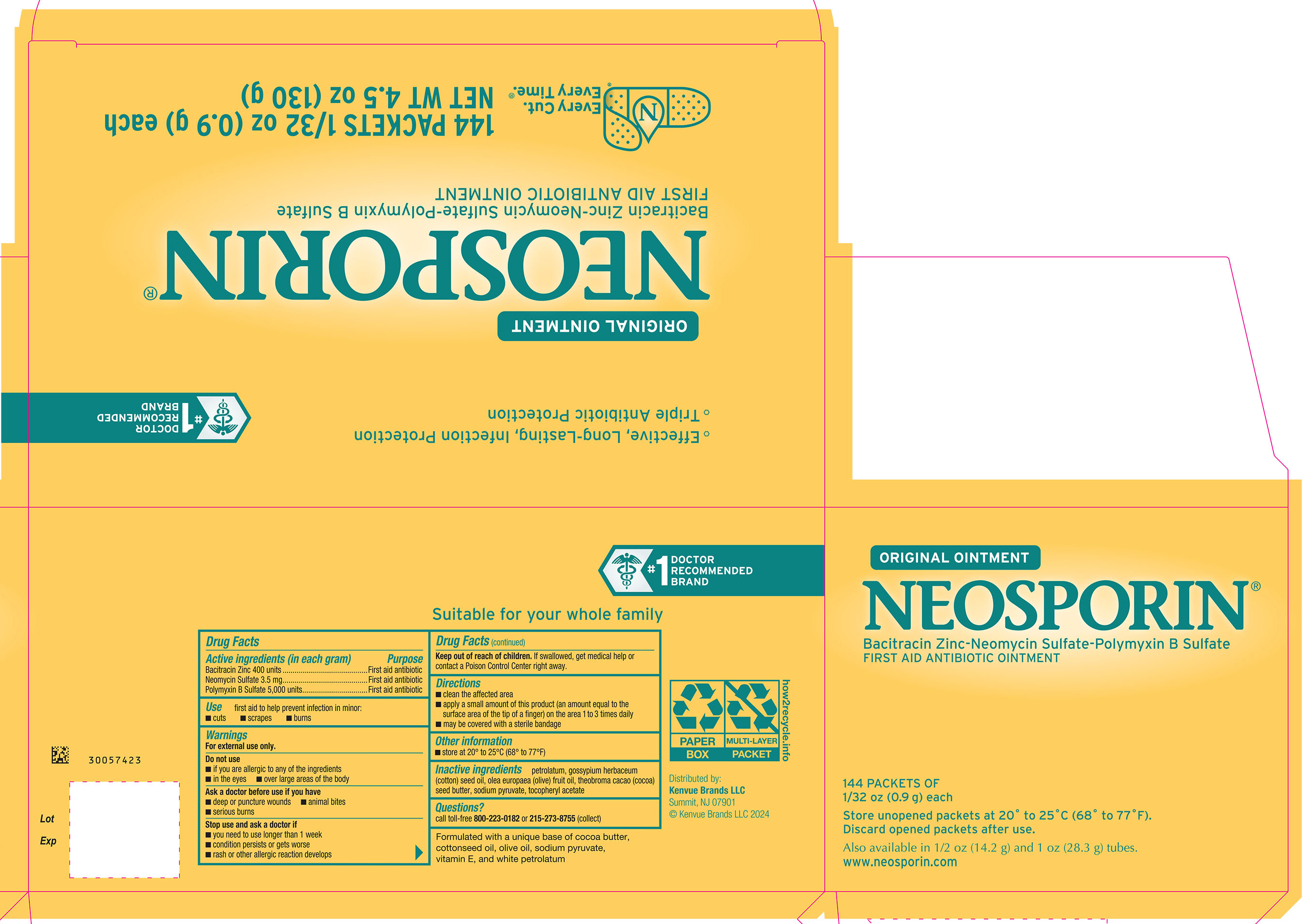 DRUG LABEL: Neosporin Original
NDC: 69968-0634 | Form: OINTMENT
Manufacturer: Kenvue Brands LLC
Category: otc | Type: HUMAN OTC DRUG LABEL
Date: 20241114

ACTIVE INGREDIENTS: BACITRACIN ZINC 400 [iU]/1 g; NEOMYCIN SULFATE 3.5 mg/1 g; POLYMYXIN B SULFATE 5000 [iU]/1 g
INACTIVE INGREDIENTS: SODIUM PYRUVATE; .ALPHA.-TOCOPHEROL ACETATE; PETROLATUM; LEVANT COTTONSEED OIL; OLIVE OIL; COCOA BUTTER

NEOSPORIN® ORIGINAL OINTMENT

Drug Facts

ACTIVE INGREDIENT

Active ingredients (in each gram) | Purpose
Bacitracin Zinc 400 units | First aid antibiotic
Neomycin Sulfate 3.5 mg | First aid antibiotic
Polymyxin B sulfate 5,000 units | First aid antibiotic

Use

first aid to help prevent infection in minor:

- cuts
- scrapes
- burns

Warnings

For external use only.

Do not use

- if you are allergic to any of the ingredients
- in the eyes
- over large areas of the body

Ask a doctor before use if you have

- deep or puncture wounds
- animal bites
- serious burns

Stop use and ask a doctor if

- you need to use longer than 1 week
- condition persists or gets worse
- rash or other allergic reaction develops

Keep out of reach of children. If swallowed, get medical help or contact a Poison Control Center right away.

Directions

- clean the affected area
- apply a small amount of this product (an amount equal to the surface area of the tip of a finger) on the area 1 to 3 times daily
- may be covered with a sterile bandage

Other information

- store at 20° to 25°C (68° to 77° F)

Inactive ingredients

petrolatum, gossypium herbaceum (cotton) seed oil, olea europaea (olive) fruit oil, theobroma cacao (cocoa) seed butter, sodium pyruvate, tocopheryl acetate

Questions?

call toll-free 800-223-0182 or 215-273-8755 (collect)

Distributed by:
Kenvue Brands LLC
Summit, NJ 07901

PRINCIPAL DISPLAY PANEL - 0.9 g Packet Carton

#1
DOCTOR
RECOMMENDED
BRAND

- Effective, Long-Lasting, Infection Protection
- Triple Antibiotic Protection

ORIGINAL OINTMENT

NEOSPORIN®

Bacitracin Zinc-Neomycin Sulfate-Polymyxin B Sulfate

FIRST AID ANTIBIOTIC OINTMENT

Every Cut.
Every Time.®

144 PACKETS 1/32 oz (0.9 g) each

NET WT 4.5 oz (130 g)